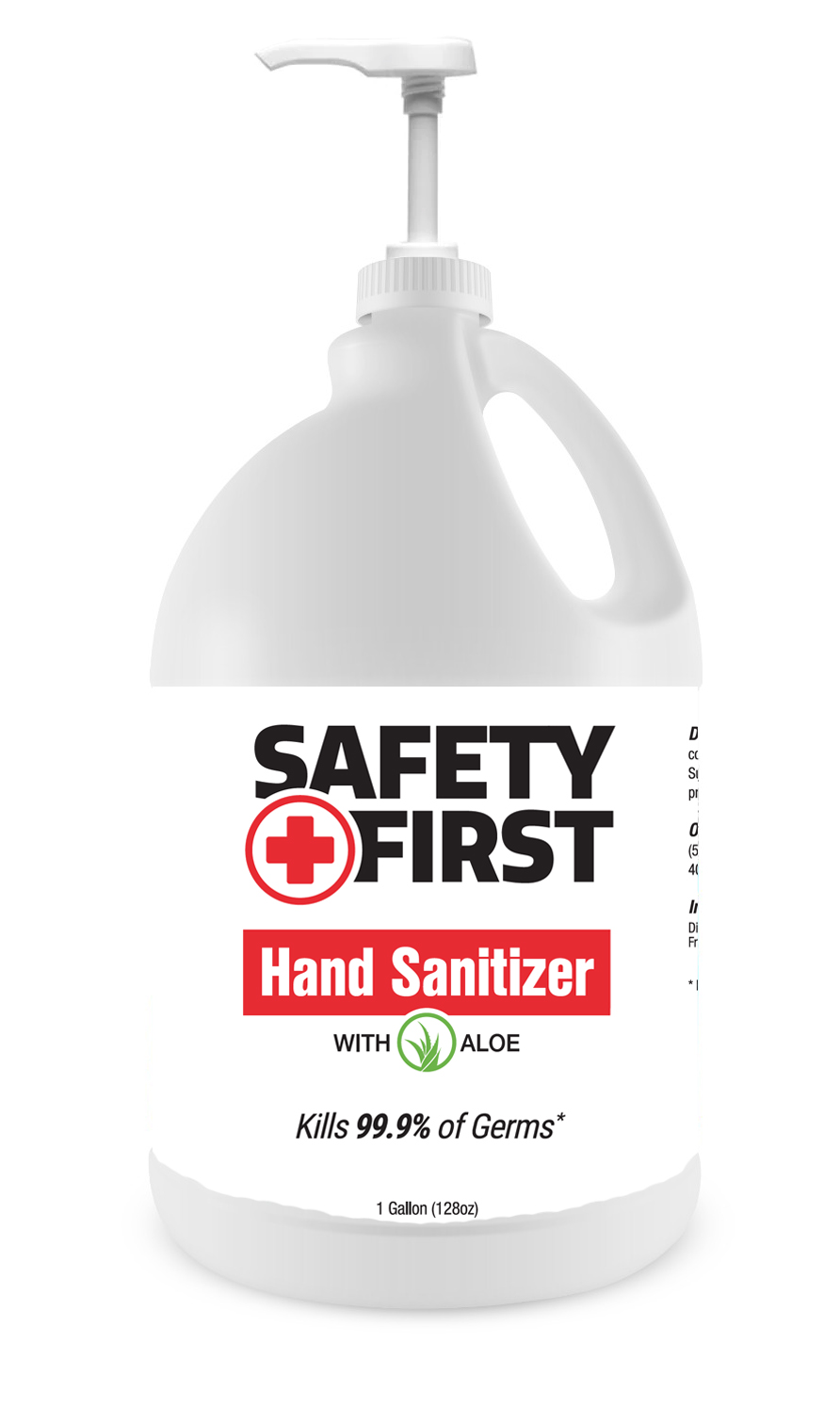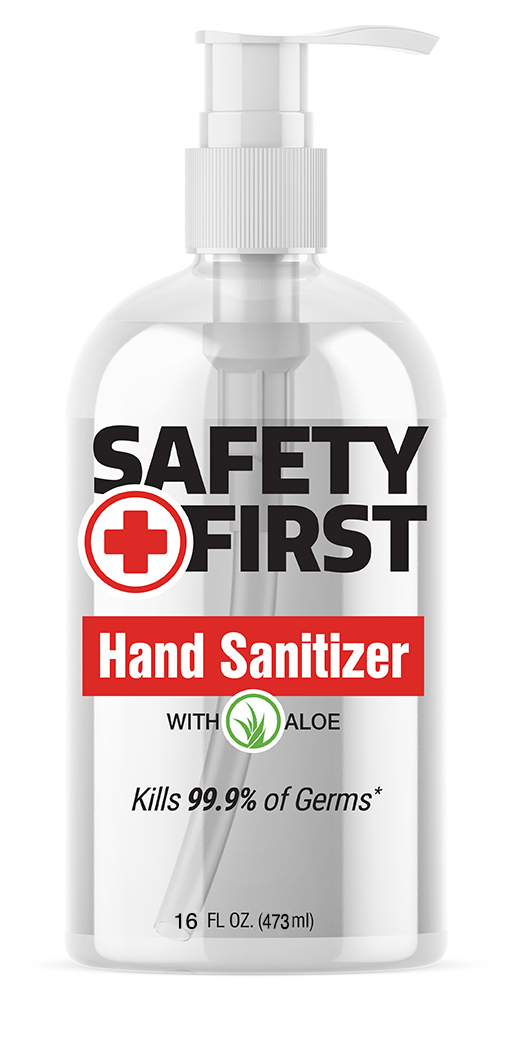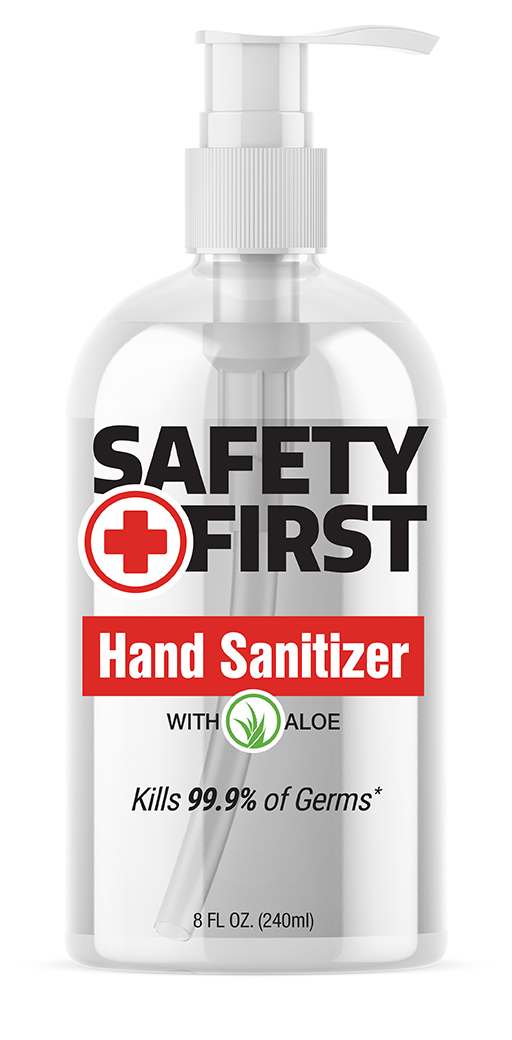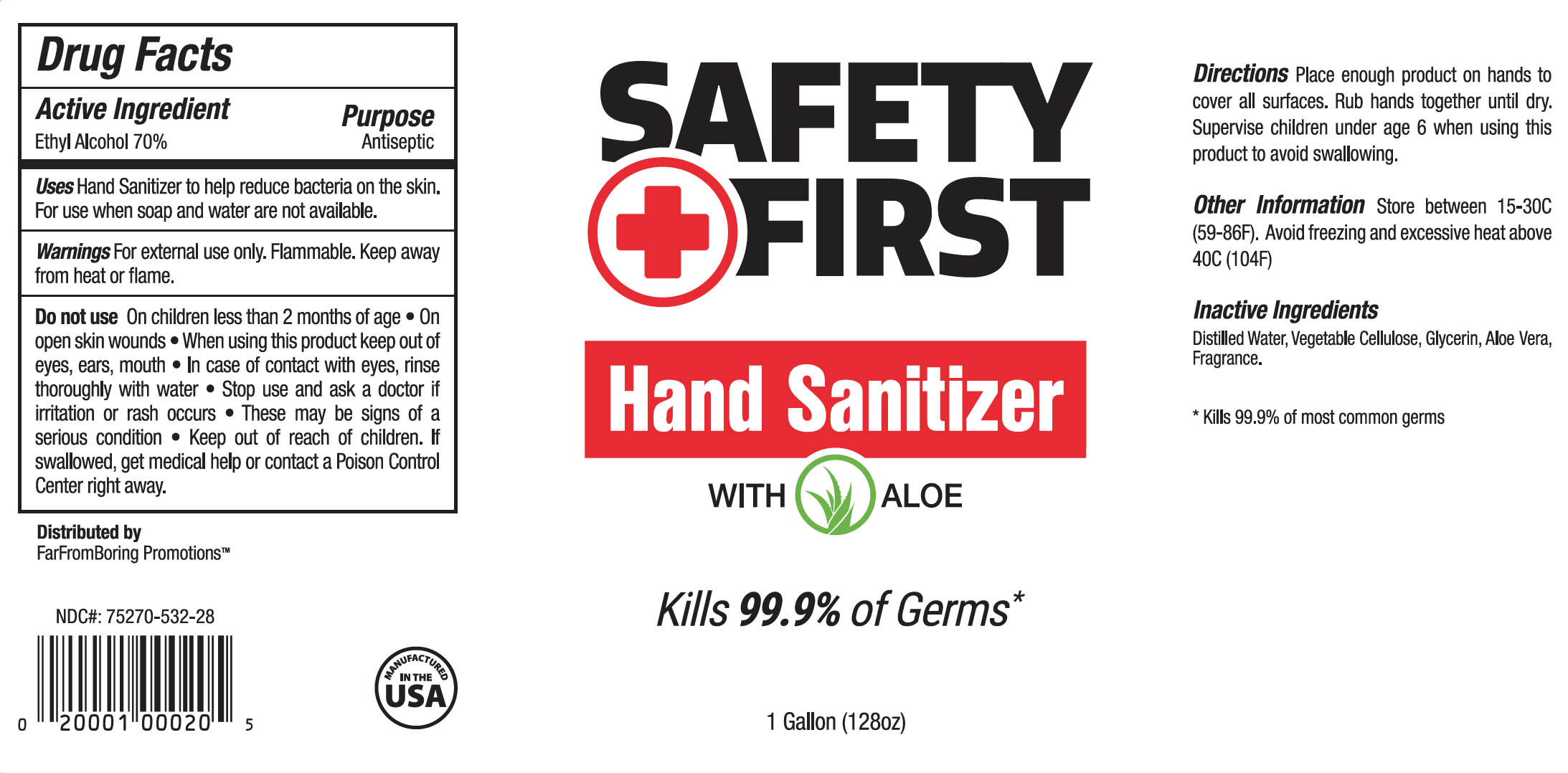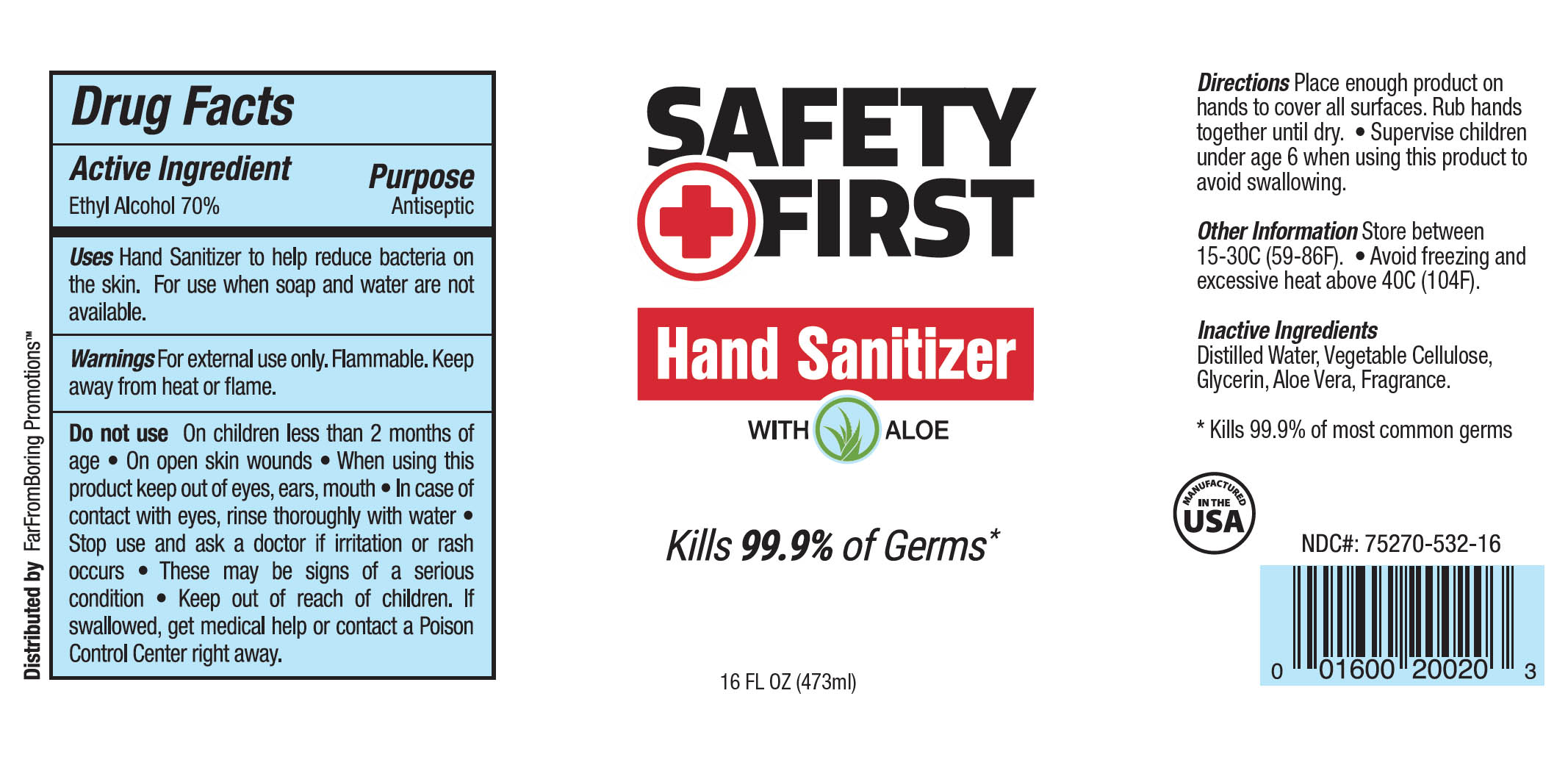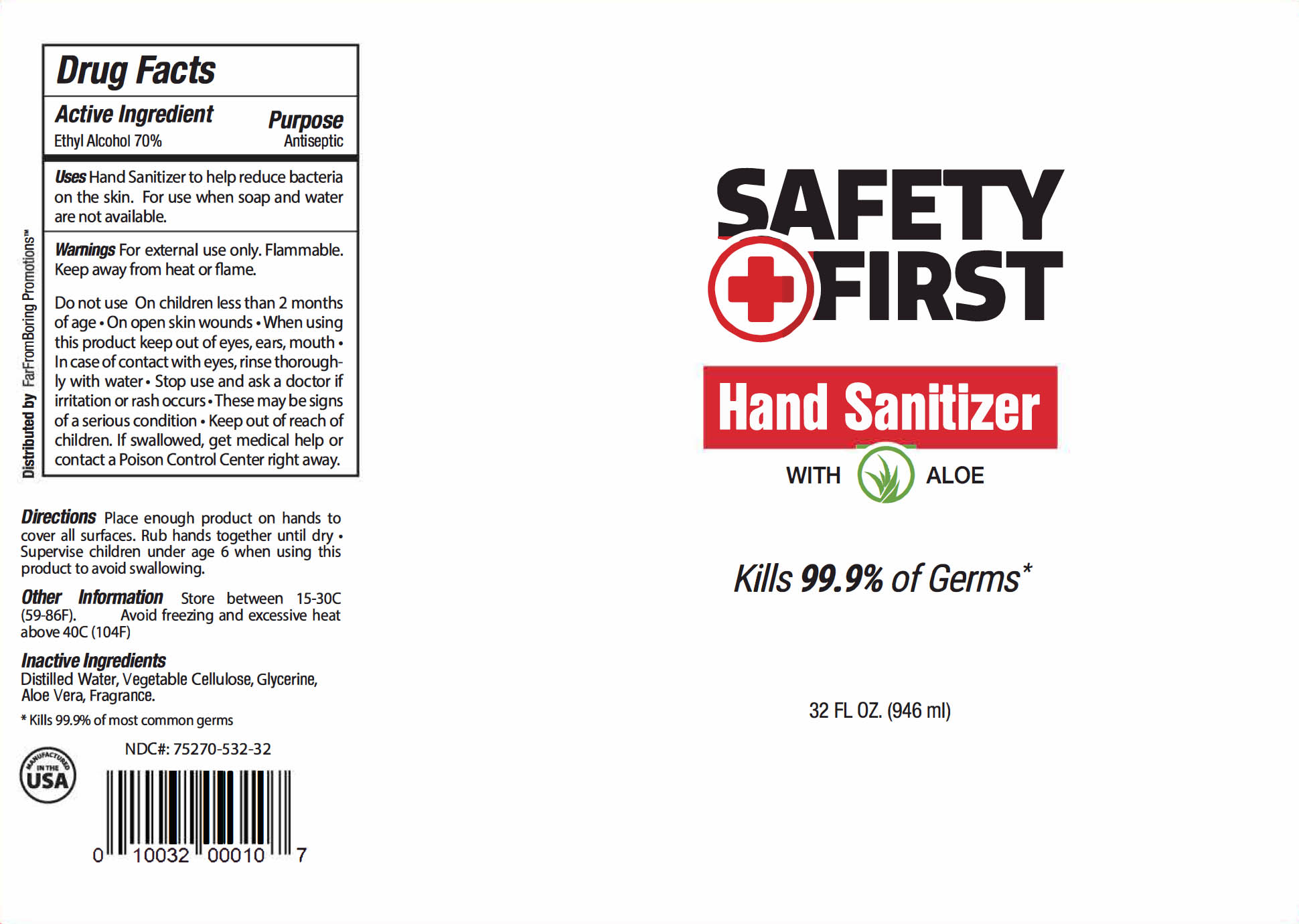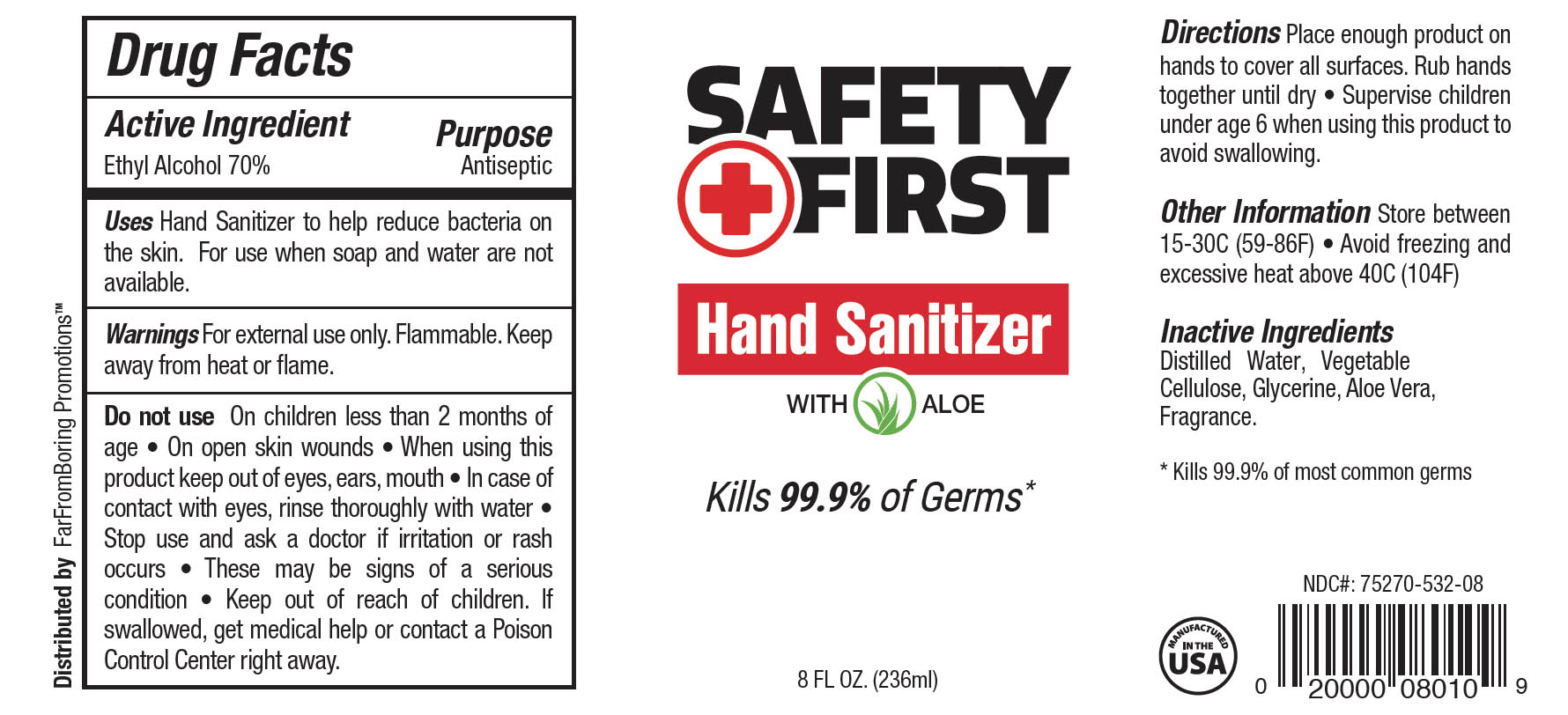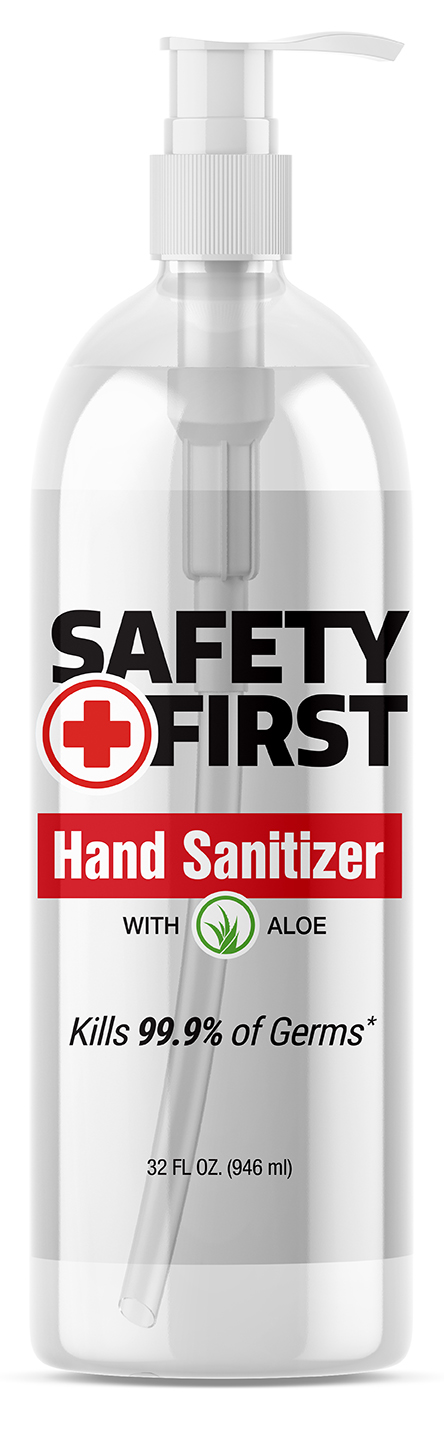 DRUG LABEL: Safety First Hand Sanitizer 70% EtOH
NDC: 75270-532 | Form: GEL
Manufacturer: LifeTech Pharma, LLC
Category: otc | Type: HUMAN OTC DRUG LABEL
Date: 20210101

ACTIVE INGREDIENTS: ALCOHOL 70.7 mL/100 mL
INACTIVE INGREDIENTS: ALOE VERA LEAF POLYSACCHARIDES 0.01 mL/100 mL; LIMONENE, (+)- 0.1 mL/100 mL; HYDROXYPROPYL CELLULOSE, UNSPECIFIED 0.01 mL/100 mL; WATER 28.5 mL/100 mL; GLYCERIN 0.7 mL/100 mL

Hand Sanitizer

This hand Sanitizer was manufactured according to the Federal Register 21 CFR 310, utilizing:

a. USP/FCC grade Ethyl alcohol 99%

b. Distilled/purified water

c. Hydroxypropylcellulose (as Vegetable Cellulose)

d. Glycerin USP/FCC grade

e. Limonene (as fragrance)

f. Aloe Vera extract

Active Ingredient(s)

Ethyl alcohol 70%

Purpose

Antiseptic, Hand Sanitizer

Uses

Decreases bacteria on skin.

Warnings

For external use only. Flammable, keep away from flames.

When using this product keep out of eyes. In case of contact, flush eyes with water.

Stop use

Stop use and ask doctor if irritation and redness develop.

Keep out of reach

Keep out of the reach of children. If swallowed, get medical help or contact a Poison Control Center right away.

Directions

• Rub hands thoroughly with product and allow to dry.
• For children under 6, use only under adult supervision.

Other Information

• Store below 110ºF (43ºC).
• May discolor certain fabrics or surfaces.

Inactive ingredients

Inactive ingredients Distilled Water,
Vegetable Cellulose,
Glycerin, Aloe Vera, Fragrance.

8 oz Packaging & Label - Principal Display Panel

8 FL Oz (236 mL) - NDC: 75270-532-08

16 oz Packaging & Label - Principal Display Panel

16 FL Oz (473 mL) - NDC: 75270-532-16

32 oz Packaging & Label - Principal Display Panel

32 FL Oz (946 mL) - NDC: 75270-532-32

128 oz Packaging & Label - Principal Display Panel

1 Gallon (3.78 L) 128 FL Oz - NDC: 75270-105-28